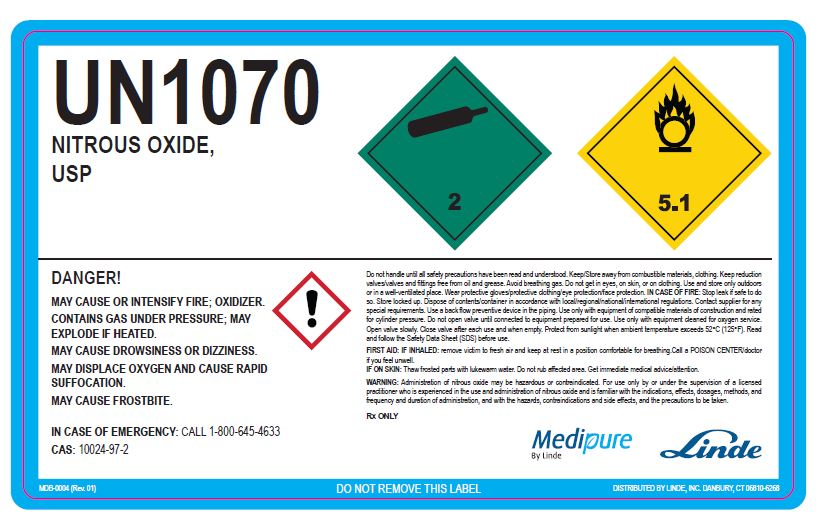 DRUG LABEL: NITROUS OXIDE
NDC: 59579-004 | Form: GAS
Manufacturer: Linde Gas & Equipment Inc.
Category: prescription | Type: HUMAN PRESCRIPTION DRUG LABEL
Date: 20250122

ACTIVE INGREDIENTS: NITROUS OXIDE 990 mL/1 L

Nitrous Oxide

NITROUS OXIDE USP LABEL

UN1070

NITROUS OXIDE, USP

DANGER!

MAY CAUSE OR INTENSIFY FIRE; OXIDIZER.

CONTAINS GAS UNDER PRESSURE; MAY EXPLODE IF HEATED.

MAY CAUSE DROWSINESS OR DIZZINESS.

MAY DISPLACE OXYGEN AND CAUSE RAPID SUFFOCATION.

MAY CAUSE FROSTBITE.

IN CASE OF EMERGENCY: CALL 1-800-645-4633

CAS: 10024-97-2

Do not handle until all safety precautions have been read and understood. Keep/Store away from combustible materials, clothing. Keep reduction valves/valves and fittings free from oil and grease. Avoid breathing gas. Do not get in eyes, on skin, or on clothing. Use and store only outdoors or in a well-ventilated place. Wear protective gloves/protective clothing/eye protection/face protection. IN CASE OF FIRE: Stop leak if safe to do so. Store locked up. Dispose of contents/container in accordance with local/regional/national/international regulations. Contact supplier for any special requirements. Use a backflow preventative device in the piping. Use only with equipment of compatible materials of construction and rated for cylinder pressure. Do not open valve until connected to equipment prepared for use. Use only with equipment cleaned for oxygen service. Open valve slowly. Close valve after each use and when empty. Protect from sunlight when ambient temperature exceeds 52°C (125°F). Read and follow the Safety Data Sheet (SDS) before use.

FIRST AID: IF INHALED: remove victim to fresh air and keep at rest in a position comfortable for breathing. Call a POISON CENTER/doctor is you feel unwell.

IF ON SKIN: Thaw frosted parts with lukewarm water. Do you rub affected area. Get immediate medical advice/attention.

WARNING! Administration of nitrous oxide may be hazardous or contraindicated. For use only by or under supervision of a licensed practitioner who is experienced in the use and administration of nitrous oxide and is familiar with the indications, effects, dosages, methods, and frequency and duration of administration, and with the hazards, contraindications, and side effects and the precautions to be taken.

Rx ONLY

Medipure by Linde

Linde

MDB-0004 (Rev. 01) DO NOT REMOVE THIS LABEL DISTRIBUTED BY LINDE, INC. DANBURY, CT 06810-6268